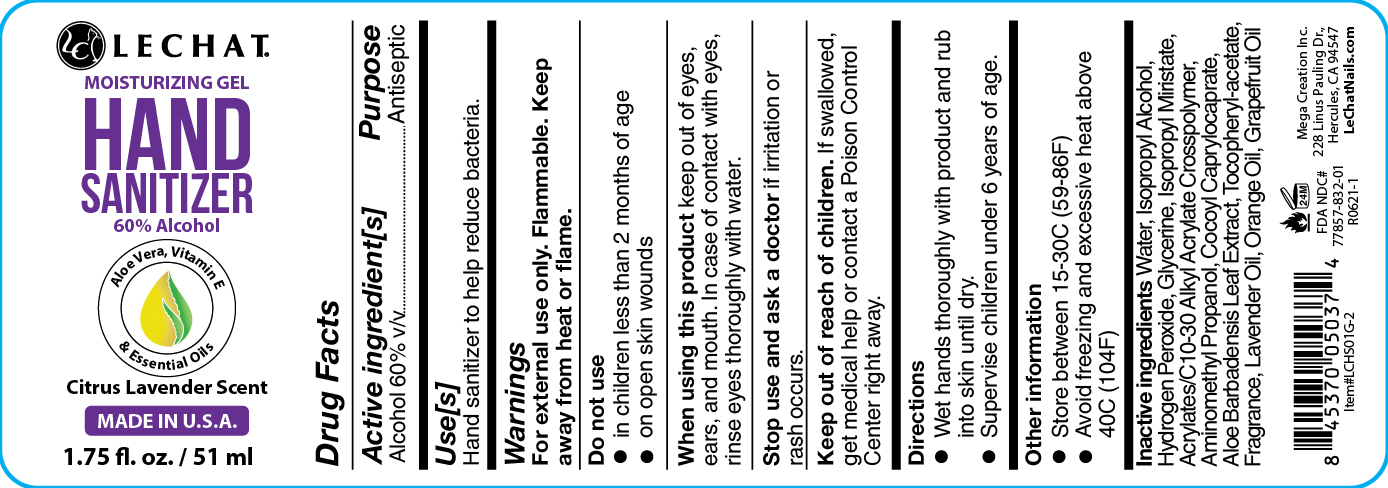 DRUG LABEL: LECHAT
NDC: 77857-832 | Form: GEL
Manufacturer: Mega Creation Inc.
Category: otc | Type: HUMAN OTC DRUG LABEL
Date: 20211110

ACTIVE INGREDIENTS: ALCOHOL 60 mL/100 mL
INACTIVE INGREDIENTS: GLYCERIN; HYDROGEN PEROXIDE; WATER; ALOE VERA LEAF; LAVENDER OIL; GRAPEFRUIT OIL; FRAGRANCE GREEN APPLE ORC2001072; ISOPROPYL ALCOHOL; CARBOMER INTERPOLYMER TYPE A (ALLYL SUCROSE CROSSLINKED); ISOPROPYL MYRISTATE; AMINOMETHYLPROPANOL; ALPHA-TOCOPHEROL ACETATE; COCO-CAPRYLATE/CAPRATE; ORANGE OIL

LECHAT Sanitizer Gel New 60% Ethanol

Active Ingredient(s)

Ethyl Alcohol 60% v/v. Purpose: Antiseptic

Purpose

Antiseptic, Hand Sanitizer

Use

Hand Sanitizer to help reduce bacteria.

Warnings

For external use only. Flammable. Keep away from heat or flame

Do not use

- in children less than 2 months of age
- on open skin wounds

When using this product keep out of eyes, ears, and mouth. In case of contact with eyes, rinse eyes thoroughly with water.
Stop use and ask a doctor if irritation or rash occurs. These may be signs of a serious condition.
Keep out of reach of children. If swallowed, get medical help or contact a Poison Control Center right away.

Stop use and ask a doctor if irritation or rash occurs. These may be signs of a serious condition.

Keep out of reach of children. If swallowed, get medical help or contact a Poison Control Center right away.

Directions

- Wet hands thoroughly with the product and rub into the skin till dry.
- Supervise children under 6 years of age when using this product to avoid swallowing.

Other information

- Store between 15-30C (59-86F)
- Avoid freezing and excessive heat above 40C (104F)

Inactive ingredients

Purified Water, IsopiopylAlcohol, Hydrogen Peroxide, Glycerin, Isopropyl Myristate, Acrylates/C10-30 Ally Acrylate Crosspolymer, Aminomethyl Propanol, Cocoyl Caprylocaprate, Aloe Barbadensis Leaf Extract, Tocopheryl-acetate, fragrance, Lavender Oil, Orange Oil, Grapefruit Oil

Package Label - Principal Display Panel

51 mL NDC: 77857-832-01